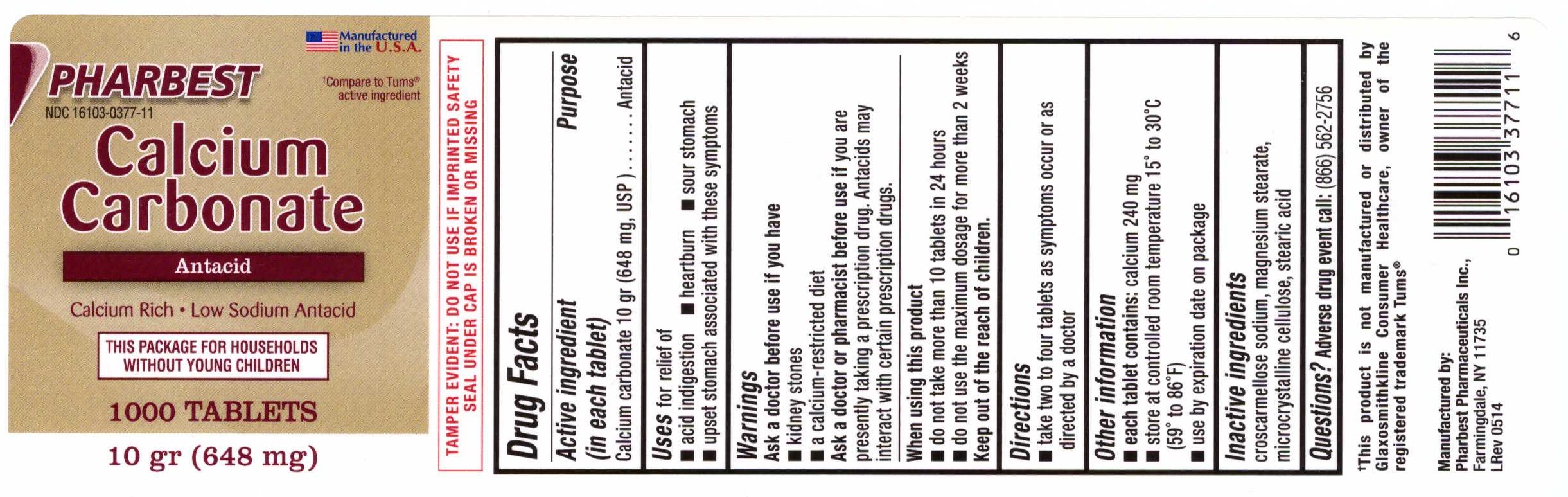 DRUG LABEL: Calcium Carbonate
                
NDC: 16103-377 | Form: TABLET
Manufacturer: Pharbest Pharmaceuticals Inc.
Category: otc | Type: HUMAN OTC DRUG LABEL
Date: 20210111

ACTIVE INGREDIENTS: CALCIUM CARBONATE 648 mg/1 1
INACTIVE INGREDIENTS: CROSCARMELLOSE SODIUM; MAGNESIUM STEARATE; CELLULOSE, MICROCRYSTALLINE; STEARIC ACID

Drug Facts

Active ingredient (in each tablet)

Calcium carbonate 10 gr (648 mg, USP)

Purpose

Antacid

Uses

for relief of

- acid indigestion
- heartburn
- sour stomach
- upset stomach associated with these symptoms

Warnings

Ask a doctor before use if you have

- kidney stone
- a calcium-restricted diet

Ask a doctor or pharmacist before use if

you are presently taking a prescription drug. Antacids may interact with certain prescription drugs.

When using this prouct

- do not take more than 10 tablets in 24 hours
- do not use the maximum dosage for more than 2 weeks

Direction

- take two to four tablets as symptoms occur or as directed by a doctor

Other information

- each tablet contains: calcium 240 mg
- store at controlled room temperature 15^0 to 30^0C (59^0 to 86^0F)
- use by expiration date on package

Inactive ingredients

croscarmellose sodium, magnesium stearate, microcrystalline cellulose, stearic acid

Questions? Adverse drug event call:

(866) 562-2756

PACKAGE LABEL

PHARBEST

NDC 16103-0377-11

Manufactured in the U.S.A.

†Compare to Tums® active ingredient

Calcium

Carbonate

Antacid

Calcium Rich •Low Sodium Antacid

THIS PACKAGE FOR HOUSEHOLDS

WITHOUT YOUNG CHILDREN

1000 TABLETS

10 gr (648 mg)